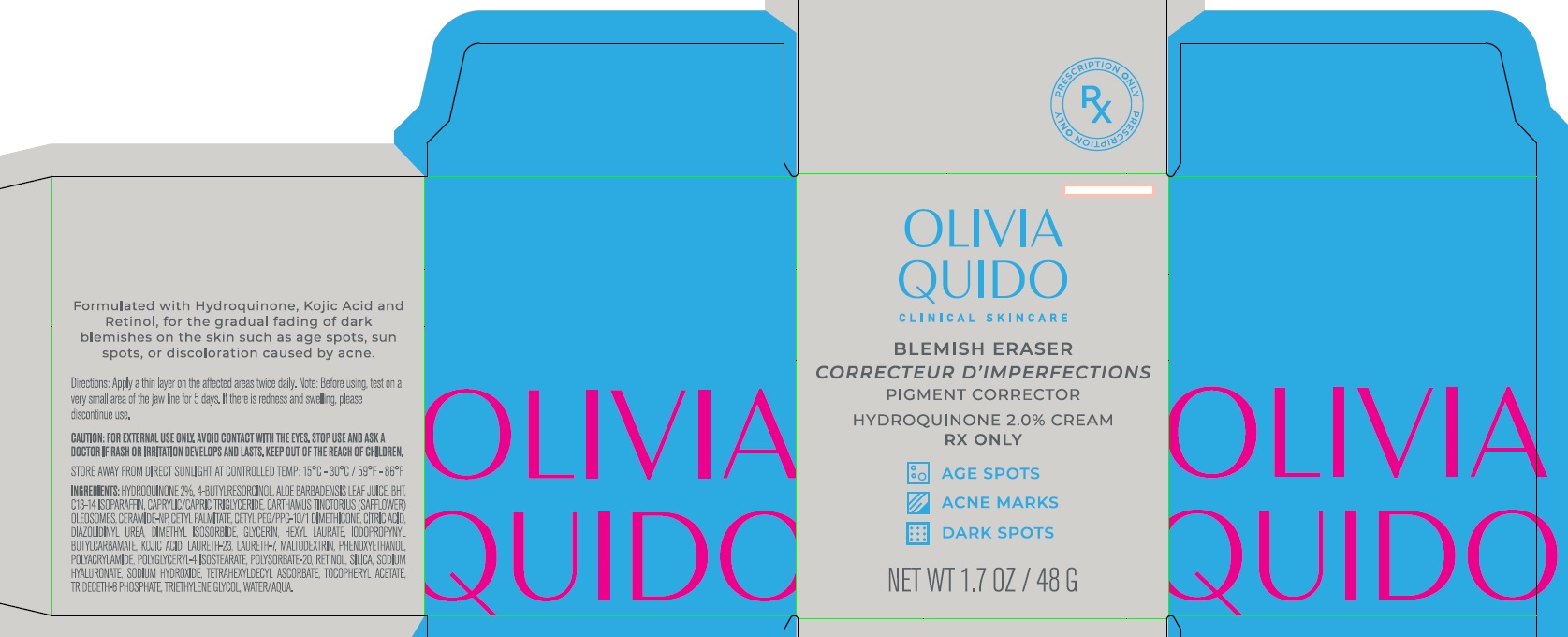 DRUG LABEL: OLIVIA QUIDO BLEMISH ERASER
NDC: 71421-801 | Form: CREAM
Manufacturer: O Skin Care LLC
Category: prescription | Type: HUMAN PRESCRIPTION DRUG LABEL
Date: 20220605

ACTIVE INGREDIENTS: HYDROQUINONE 0.02 g/1 g
INACTIVE INGREDIENTS: CARTHAMUS TINCTORIUS (SAFFLOWER) OLEOSOMES; BUTYLATED HYDROXYTOLUENE; IODOPROPYNYL BUTYLCARBAMATE; C13-14 ISOPARAFFIN; GLYCERIN; MALTODEXTRIN; HYALURONIC ACID; PHENOXYETHANOL; POLYACRYLAMIDE (1500 MW); POLYSORBATE 20; TETRAHEXYLDECYL ASCORBATE; WATER; TRIETHYLENE GLYCOL; ALOE VERA LEAF; DIAZOLIDINYL UREA; DIMETHYL ISOSORBIDE; LAURETH-7; CERAMIDE NP; TRIDECETH-6 PHOSPHATE; CETYL PALMITATE; HEXYL LAURATE; KOJIC ACID; RETINOL; 4-BUTYLRESORCINOL; CETYL PEG/PPG-10/1 DIMETHICONE (HLB 2); ANHYDROUS CITRIC ACID; POLYGLYCERYL-4 ISOSTEARATE

HIGHLIGHTS OF PRESCRIBING INFORMATION

These highlights do not include all the information needed to use BLEMISH ERASER safely and effectively. See full prescribing information for BLEMISH ERASER.
OLIVIA QUIDO FIRM & FADE I Cream (hydrocortisone, hydroquinone, tretinoin) cream, 1%/8%/0.1% for topical use. for topical use
Initial U.S. Approval: XXXX

BLEMISH ERASER is a hydroquinone (a melanin synthesis inhibitor) that is indicated for the gradual bleaching of hyperpigmented skin conditions age and liver spots, freckles, and other unwanted areas of melanin hyperpigmentation, in the presence of measures for sun avoidance, including the use of sunscreen. (1)

2 DOSAGE AND ADMINISTRATION
Gently wash the face and neck with a mild cleanser. Rinse and pat the skin dry. Apply a thin film of BLEMISH ERASER to the affected area once daily at night or as directed by a doctor.
During the day, use O Skin Sunscreen SPF-50, and wear protective clothing. Avoid sunlight exposure to prevent repigmentation.
BLEMISH ERASER is for topical use only. It is not for oral, ophthalmic, or intravaginal use.

Cream, 2%.

Each gram of BLEMISH ERASER contains 20.0 mg of hydroquinone in a cream base. (3)

CONTRAINDICATIONS

BLEMISH ERASER is contraindicated in individuals with a history of hypersensitivity to this product or any of its components.. (4)

If anaphylaxis, asthma or other clinically significantly hypersensitivity reactions occur, institute appropriate therapy and discontinue BLEMISH ERASER. Allergic contact dermatitis may also occur. (5.1)
BLEMISH ERASER contains hydroquinone, which may produce exogenous ochronosis, a gradual blue-black darkening of the skin, the occurrence of which should prompt discontinuation of therapy. (5.2)

ADVERSE REACTIONS

In case of adverse reaction, call a doctor. (6)

To report SUSPECTED ADVERSE REACTIONS, contact FDA at 1-800-FDA-1088 or www.fda.gov/medwatch.

BLEMISH ERASER should be used during pregnancy only if the potential benefit justifies the potential risk to the fetus. (8.1)

FULL PRESCRIBING INFORMATION

INDICATIONS AND USAGE

1.1Indication

BLEMISH ERASER is a combination of hydrocortisone (a corticosteroid), hydroquinone (a melanin synthesis inhibitor), and a tretinoin (a retinoid) that is indicated for the gradual bleaching of hyperpigmented skin conditions age and liver spots, freckles, and other unwanted areas of melanin hyperpigmentation, in the presence of measures for sun avoidance, including the use of sunscreen.

1.2 Limitations of Use

The safety and efficacy of BLEMISH ERASER in pregnant women and nursing mothers have not been established.

2 DOSAGE AND ADMINISTRATION
Gently wash the face and neck with a mild cleanser. Rinse and pat the skin dry. Apply a thin film of BLEMISH ERASER to the affected area once daily at night or as directed by a doctor.
During the day, use O Skin Sunscreen SPF-50, and wear protective clothing. Avoid sunlight exposure to prevent repigmentation.
BLEMISH ERASER is for topical use only. It is not for oral, ophthalmic, or intravaginal use.

3 DOSAGE FORMS AND STRENGTHS

Cream, 2%.

Each gram of BLEMISH ERASER contains 20.0 mg of hydroquinone in a cream base. (3)

CONTRAINDICATIONS

BLEMISH ERASER is contraindicated in individuals with a history of hypersensitivity to this product or any of its components.. (4)

5 WARNINGS AND PRECAUTIONS

5.1 Hypersensitivity

If anaphylaxis, asthma or other clinically significantly hypersensitivity reactions occur, institute appropriate therapy and discontinue BLEMISH ERASER. Allergic contact dermatitis may also occur.

Since this product contains no sunscreen, an effective broad spectrum sun blocking agent should be used and unnecessary solar exposure avoided, or protective clothing should be worn to cover bleached skin in order to prevent repigmentation from occurring.

5.2 Exogenous Ochronosis
BLEMISH ERASER contains hydroquinone, which may produce exogenous ochronosis, a gradual blue-black darkening of the skin, the occurrence of which should prompt discontinuation of therapy. Most patients developing this condition are Black, but it may also occur in Caucasians and Hispanics.

5.3. Effects on Endocrine System

Manifestations of Cushing’s syndrome, hyperglycemia, and glucosuria can also be produced by systemic absorption of topical corticosteroid while treatment. If HPA axis suppression is noted, the use of BLEMISH ERASER should be discontinued. Recovery of HPA axis function generally occurs upon discontinuation of topical corticosteroids.

5.4 Cutaneous Reactions
BLEMISH ERASER contains hydroquinone that may cause mild to moderate irritation. Local irritation, such as skin reddening, peeling, mild burning sensation, dryness, and pruritus may be expected at the site of application. Transient skin reddening or mild burning sensation does not preclude treatment. If a reaction suggests hypersensitivity or chemical irritation, discontinue use of the medication and call a doctor.
Patients should avoid medicated or abrasive soaps and cleansers, soaps and cosmetics with drying effects, products with high concentrations of alcohol and astringents, and other irritants or keratolytic drugs while on BLEMISH ERASER treatment. Avoid use of medications that are known to be photosensitizing.

ADVERSE REACTIONS

No systemic adverse reactions have been reported. Occasional hypersensitivity (localized contact dermatitis) may occur, in which case the medication should be discontinued and the physician notified immediately.

7 DRUG INTERACTIONS
Patients should avoid medicated or abrasive soaps and cleansers, soaps and cosmetics with drying effects, products with high concentration of alcohol and astringent, and other irritants or keratolytic drugs while on BLEMISH ERASER Cream treatment. Patients are cautioned on concomitant use of medications that are known to be photosensitizing.

8 USE IN SPECIFIC POPULATIONS

8.1 Pregnancy

Teratogenic Effects: Pregnancy Category C

In general, use of drugs should be reduced to a minimum in pregnancy. If a patient has been inadvertently exposed to BLEMISH ERASER in pregnancy, she should be counseled on the risk of teratogenesis due to this exposure. The risk of teratogenesis due to topical exposure to BLEMISH ERASER may be considered low. However, exposure during the period of organogenesis in the first trimester is theoretically more likely to produce adverse outcome than in later pregnancy.

8.3 Nursing Mothers

Corticosteroids, when systemically administered, appear in human milk. It is not known whether topical application of BLEMISH ERASER could result in sufficient systemic absorption to produce detectable quantities of hydroquinone in human milk. Because many drugs are secreted in human milk, caution should be exercised when BLEMISH ERASER is administered to a nursing woman. Care should be taken to avoid contact between the infant being nursed and BLEMISH ERASER.
8.4 Pediatric Use

Safety and effectiveness of BLEMISH ERASER in pediatric patients have not been established.

8.5 Geriatric Use

In general, dose selection for an elderly patient should be cautious, usually starting at the low end of the dosing range, reflecting the greater frequency of decreased hepatic, renal or cardiac function, and of concomitant disease or other drug therapy.

10 OVERDOSAGE

There have been no systemic reactions reported from the use of topical hydroquinone. However, treatment should be limited to relatively small areas of the body at one time, since some patients experience a transient skin reddening and a mild burning sensation which does not preclude treatment.

11 DESCRIPTION

BLEMISH ERASER contains 2% of hydroquinone, USP, in a cream base for topical application.

Hydroquinone is a melanin synthesis inhibitor. It is prepared from the reduction of p-benzoquinone with sodium bisulfite. It occurs as fine white needles that darken on exposure to air. The chemical name for hydroquinone is: 1,4-benzenediol. The molecular formula is C6H6O2 and molecular weight is 110.11. Hydroquinone has the following structural formula:

BLEMISH ERASER contains Active: 2% (20 mg) Hydroquinone. Inactive: 4-Butylresorcinol, Aloe Barbadensis Leaf Juice, BHT, C13-14 Isoparaffin, Caprylic/Capric Triglyceride, Carthamus Tinctorius (Safflower) Oleosomes, Ceramide-NP, Cetyl Palmitate, Cetyl PEG/PPG-10/1 Dimethicone, Citric Acid, Diazolidinyl Urea, Dimethyl Isosorbide, Glycerin, Hexyl Laurate, Iodopropynyl Butylcarbamate, Kojic Acid, Laureth-23, Laureth-7, Maltodextrin, Phenoxyethanol, Polyacrylamide, Polyglyceryl-4 Isostearate, Polysorbate 20, Retinol, Silica, Sodium Hyaluronate, Sodium Hydroxide, Tetrahexyldecyl Ascorbate, Tocopheryl Acetate, Trideceth-6 Phosphate, Triethylene Glycol, Water/Aqua.

12 CLINICAL PHARMACOLOGY

12.1 Mechanism of Action

The mechanism of action of the active ingredients in BLEMISH ERASER in the treatment of melasma is unknown.

13 NONCLINICAL TOXICOLOGY

13.1 Carcinogenesis, Mutagenesis, Impairment of Fertility

Carcinogenesis

Studies of hydroquinone in animals have demonstrated some evidence of carcinogenicity. The carcinogenic potential of hydroquinone in humans is unknown.

Mutagenesis

Mutagenicity studies were not conducted with this combination of active ingredients. Published studies have demonstrated that hydroquinone is a mutagen and a clastogen. Treatment with hydroquinone has resulted in positive findings for genetic toxicity in the Ames assay in bacterial strains sensitive to oxidizing mutagens, in in vitro studies in mammalian cells, and in the in vivo mouse micronucleus assay. Tretinoin has been shown to be negative for mutagenesis in the Ames assay. Additional information regarding the genetic toxicity potential of tretinoin is not available.

Impairment of Fertility

No studies of fertility and early embryonic toxicity of this drug product has been performed.

16 HOW SUPPLIED

BLEMISH ERASER is light yellow in color, and supplied in 48 g jar, NDC 71421-801-30.

STORAGE AND HANDLING

Storage: Keep tightly closed. Store at 25°C (77°F); excursions permitted to 15°C – 30°C (59°F – 86°F) away from direct sunlight. KEEP REFRIGERATED.

17 PATIENT COUNSELING INFORMATION
See FDA-approved patient labeling (Patient Information).
Inform patients of the following:
• Advise patients to change to non-hormonal forms of birth control, if hormonal methods are used.
• Use BLEMISH ERASER as directed by the health care provider and do not use BLEMISH ERASER for any disorder other than that for which it is prescribed.
• Avoid exposure to sunlight, sunlamp, or ultraviolet light. Patients who are consistently exposed to sunlight or
skin irritants either through their work environment or habits should exercise particular caution. Use sunscreen
and protective covering (such as the use of a hat) over the treated areas. Sunscreen use is an essential aspect
of melasma therapy, as even minimal sunlight sustains melanocytic activity.
• Weather extremes, such as heat or cold, may be irritating to patients treated with BLEMISH ERASER. Because of the drying effect of this medication, a moisturizer may be applied to the face in the morning after washing.
• Keep BLEMISH ERASER away from the eyes, nose, angles of the mouth, or open wounds
because these areas are more sensitive to the irritant effect. If local irritation persists or becomes severe,
discontinue application of the medication and consult your health care provider. Seek medical attention if you
experience allergic contact dermatitis, blistering, crusting, and severe burning or swelling of the skin and irritation
of the mucous membranes of the eyes, nose, and mouth.
• If the medication is applied excessively, marked redness, peeling, or discomfort may occur.
• Wash your hands after each application.